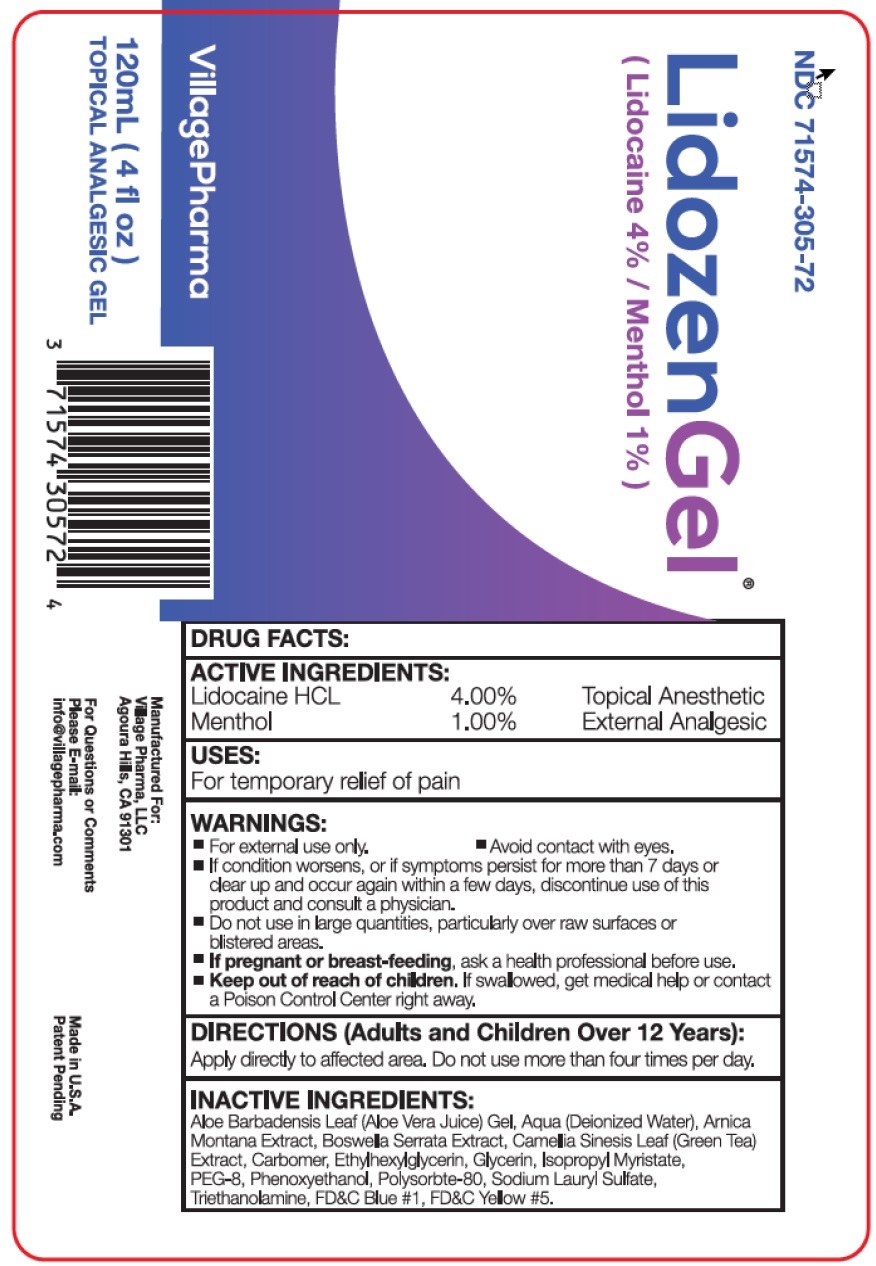 DRUG LABEL: Lidozen Gel
NDC: 71574-305 | Form: GEL
Manufacturer: Village Pharma LLC
Category: otc | Type: HUMAN OTC DRUG LABEL
Date: 20260101

ACTIVE INGREDIENTS: LIDOCAINE HYDROCHLORIDE 40 mg/1 mL; MENTHOL, UNSPECIFIED FORM 10 mg/1 mL
INACTIVE INGREDIENTS: ALOE VERA LEAF; WATER; ARNICA MONTANA WHOLE; INDIAN FRANKINCENSE; GREEN TEA LEAF; CARBOMER HOMOPOLYMER, UNSPECIFIED TYPE; ETHYLHEXYLGLYCERIN; GLYCERIN; ISOPROPYL MYRISTATE; POLYETHYLENE GLYCOL 400; PHENOXYETHANOL; POLYSORBATE 80; SODIUM LAURYL SULFATE; TROLAMINE; FD&C BLUE NO. 1; FD&C YELLOW NO. 5

Lidozen Gel

ACTIVE INGREDIENTS:

Lidocaine HCL 4.00%

Menthol 1.00%

PURPOSE

Topical Anesthetic

External Analgesic

USES:

For temporary relief of pain

WARNINGS:

- For external use only.
- Avoid contact with eyes.
- If condition worsens, or if symptoms persist for more than 7 days or clear up and occur again within a few days, discontinue use of this product and consult a physician.

Do not use

- in large quantities, particularly over raw surfaces or blistered areas.

If pregnant or breast-feeding,

- ask a health professional before use.

Keep out of reach of children.

- If swallowed, get medical help or contact a Poison Control Center right away.

DIRECTIONS (Adults and Children Over 12 Years):

Apply directly to affected area. Do not use more than four times per day.

INACTIVE INGREDIENTS

Aloe Barbadensis Leaf (Aloe Vera Juice) Gel, Aqua (Deionized Water), Arnica Montana Extract, Boswellia Serrata Extract, Camellia Sinensis Leaf (Green Tea) Extract, Carbomer, Ethylhexylglycerin, Glycerin, Isopropyl Myristate, PEG-8, Phenoxyethanol, Polysorate-80, Sodium Lauryl Sulfate, Triethanolamine, FD&C Blue #1, FD&C Yellow #5.